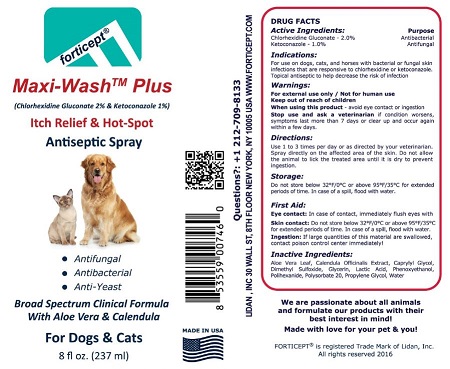 DRUG LABEL: Forticept Maxi-Wash Plus
NDC: 72127-0804 | Form: LIQUID
Manufacturer: Lidan, Inc.
Category: animal | Type: OTC ANIMAL DRUG LABEL
Date: 20220120

ACTIVE INGREDIENTS: CHLORHEXIDINE GLUCONATE 20 g/1000 g; KETOCONAZOLE 10 g/1000 g
INACTIVE INGREDIENTS: ALOE VERA LEAF; CALENDULA OFFICINALIS FLOWER; CAPRYLYL GLYCOL; DIMETHYL SULFOXIDE; GLYCERIN; LACTIC ACID; PHENOXYETHANOL; POLIHEXANIDE; POLYSORBATE 20; PROPYLENE GLYCOL; WATER

Active Ingredients:

Chlorhexidine Gluconate.......2%

Ketokonazole.......1%

Inactive ingredients:

Aloe Vera Leaf, Calendula Officinalis Extract, Caprylyl Glycol, Dimethyl Sulfoxide, Glycerin, Lactic Acid, Phenoxyethanol, Polihexanide, Polysorbate 20, Propylene Glycol, Water

Indications:

For use on dogs, cats, and horses with bacterial or fungal skin infections that are responsive to chlorhexidine or ketoconazole. Topical antiseptic to help decrease the risk of infection.

Warnings:

For external use only / Not for human use
Keep out of reach of children
When using this product - avoid eye contact or ingestion
Stop use and ask a veterinarian if condition worsens, symptoms last more than 7 days or clear up and occur again within a few days.

Directions:

Use 1 to 3 times per day or as directed by your veterinarian. Spray directly on the affected area of the skin. Do not allow the animal to lick the treated area until it is dry to prevent ingestion.

Storage:

Do not store below 32°F/0°C or above 95°F/35°C for extended periods of time. In case of a spill, flood with water.

First Aid:

Eye contact: In case of contact, immediately flush eyes with cool running water.
Skin contact: Wash the skin with water and soap. Wash clothing before reuse.
Ingestion: If large quantities of this material are swallowed, contact poison control center immediately